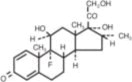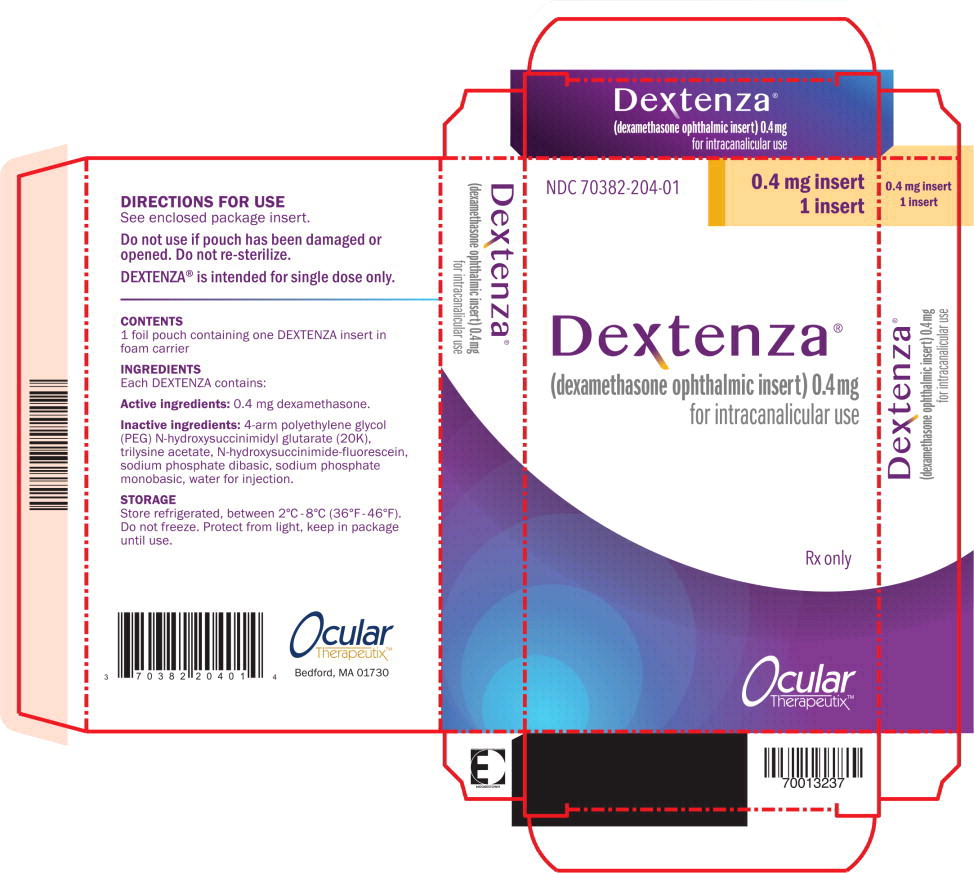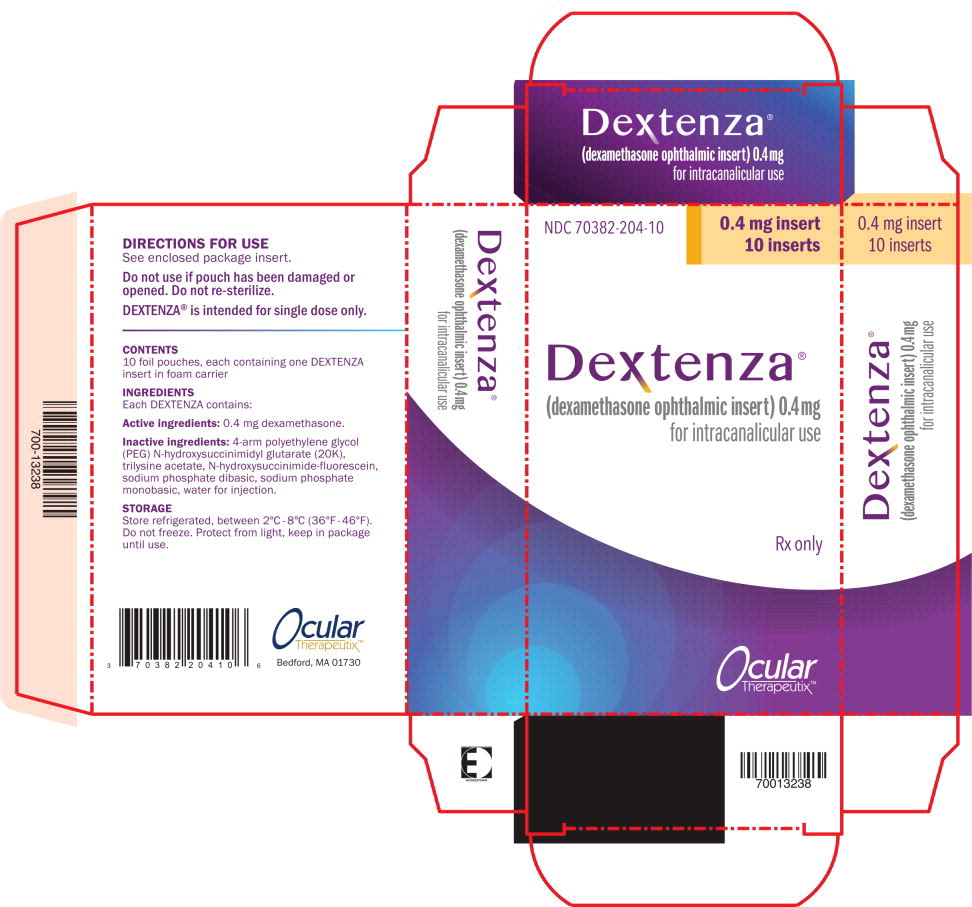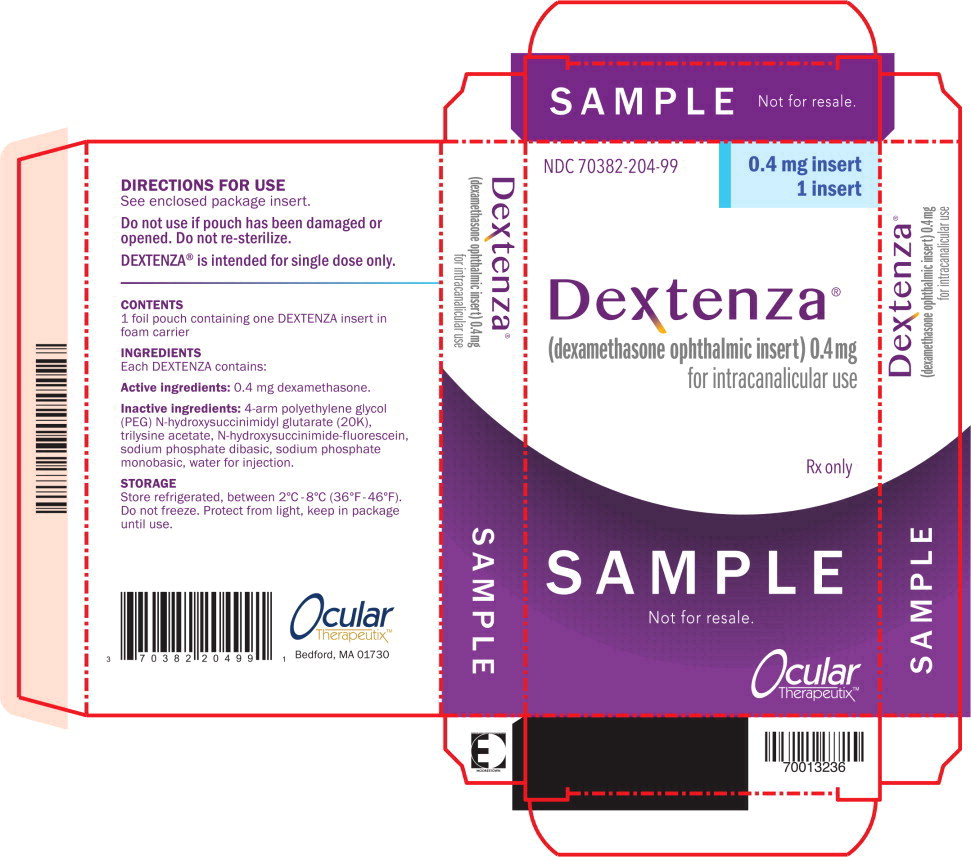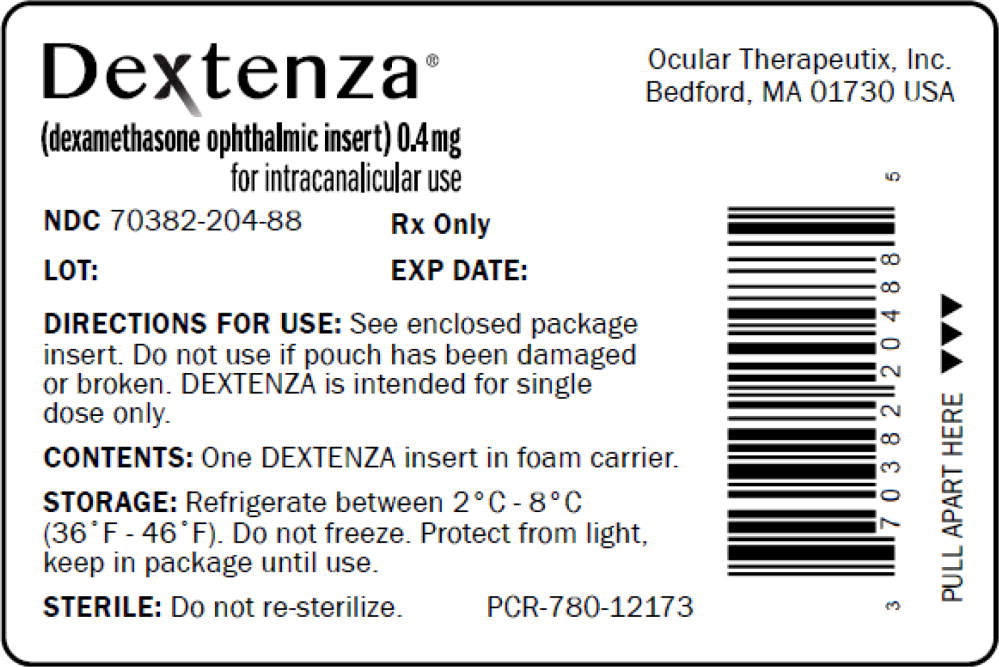 DRUG LABEL: DEXTENZA

NDC: 70382-204 | Form: INSERT
Manufacturer: Ocular Therapeutix, Inc.

Category: prescription | Type: HUMAN PRESCRIPTION DRUG LABEL
Date: 20250418

ACTIVE INGREDIENTS: dexamethasone
 0.4 mg/1 1
INACTIVE INGREDIENTS: POLYETHYLENE GLYCOL, UNSPECIFIED; LYSYLLYSYLLYSINE; FLUORESCEIN; SODIUM PHOSPHATE, DIBASIC, ANHYDROUS; SODIUM PHOSPHATE, MONOBASIC, ANHYDROUS

HIGHLIGHTS OF PRESCRIBING INFORMATION

These highlights do not include all the information needed to use DEXTENZA safely and effectively. See full prescribing information for DEXTENZA.
DEXTENZA® (dexamethasone ophthalmic insert) 0.4 mg, for intracanalicular use
Initial U.S. Approval: 1958

RECENT MAJOR CHANGES

Indications and Usage (1.1, 1.2) | 04/2025

1 INDICATIONS AND USAGE

DEXTENZA® is a corticosteroid indicated for:

- The treatment of ocular inflammation and pain following ophthalmic surgery in adults and pediatric patients. (1.1).
- The treatment of ocular itching associated with allergic conjunctivitis in adults and pediatric patients aged 2 years and older. The use of DEXTENZA is not recommended for the treatment of ocular itching associated with allergic conjunctivitis in pediatric patients who require sedation for the insertion procedure. (1.2).

2 DOSAGE AND ADMINISTRATION

DEXTENZA is an ophthalmic insert that is inserted in the lower lacrimal punctum and into the canaliculus. A single DEXTENZA releases a 0.4 mg dose of dexamethasone for up to 30 days following insertion (2).

3 DOSAGE FORMS AND STRENGTHS

Ophthalmic intracanalicular insert containing a 0.4 mg dose of dexamethasone (3).

4 CONTRAINDICATIONS

Active ocular infections (4).

5 WARNINGS AND PRECAUTIONS

- Intraocular Pressure Increase: Monitor intraocular pressure (5.1).
- Bacterial Infections: Steroids may mask signs of infections and enhance existing infections (5.2).
- Viral Infections: Ocular steroids may prolong the course and exacerbate the severity of ocular viral infections (5.3).
- Fungal Infections: Consider fungal invasion in any persistent corneal ulceration (5.4).
- Delayed Healing: Ocular steroids may slow the rate of ocular healing. (5.5).

6 ADVERSE REACTIONS

- The most commonly reported adverse reactions were anterior chamber inflammation and elevations in intraocular pressure. These occurred in approximately 6-10% of patients (6).

To report SUSPECTED ADVERSE REACTIONS, contact Ocular Therapeutix at 1-800-DEXTENZA (339-8369) or FDA at 1-800-FDA-1088 or www.fda.gov/medwatch.

FULL PRESCRIBING INFORMATION

1 INDICATIONS AND USAGE

1.1 Ocular Inflammation and Pain Following Ophthalmic Surgery

DEXTENZA is indicated for the treatment of ocular inflammation and pain following ophthalmic surgery (1.1).

1.2 Itching Associated with Allergic Conjunctivitis

DEXTENZA is indicated for the treatment of ocular itching associated with allergic conjunctivitis in adults and pediatric patients aged 2 years and older (1.2).

Limitations of Use

The use of DEXTENZA is not recommended for the treatment of ocular itching associated with allergic conjunctivitis in pediatric patients who require sedation for the insertion procedure [see Use in Specific Populations (8.4)].

2 DOSAGE AND ADMINISTRATION

2.1 General Dosing Information

DEXTENZA is an ophthalmic insert that is inserted in the lower lacrimal punctum into the canaliculus. A single DEXTENZA insert releases a 0.4 mg dose of dexamethasone for up to 30 days following insertion.

DEXTENZA is resorbable and does not require removal. Saline irrigation or manual expression can be performed to remove the insert if necessary. DEXTENZA is intended for single-use only.

2.2 Administration

Do not use if pouch has been damaged or opened. Do not re-sterilize.

1. Carefully remove foam carrier and transfer to a clean and dry area.
2. If necessary, dilate the punctum with an ophthalmic dilator. Care should be taken not to perforate the canaliculus during dilation or insertion of DEXTENZA. If perforation occurs, do not insert DEXTENZA.
3. After drying the punctal area, using blunt (non-toothed) forceps, grasp DEXTENZA and insert into the lower lacrimal canaliculus by pulling the lid temporally and inserting nasally.
4. Ensure DEXTENZA is placed just below the punctal opening. Excessive squeezing of DEXTENZA with forceps may cause deformation.
5. To aid in the hydration of DEXTENZA, 1 to 2 drops of balanced salt solution can be instilled into the punctum. DEXTENZA hydrates quickly upon contact with moisture. If DEXTENZA begins to hydrate before fully inserted, discard the product and use a new DEXTENZA.
6. DEXTENZA can be visualized when illuminated by a blue light source (e.g., slit lamp or hand held blue light) with yellow filter.

3 DOSAGE FORMS AND STRENGTHS

Ophthalmic insert: fluorescent yellow, 3 mm cylindrical-shaped insert containing dexamethasone, 0.4 mg.

4 CONTRAINDICATIONS

DEXTENZA is contraindicated in patients with active corneal, conjunctival or canalicular infections, including epithelial herpes simplex keratitis (dendritic keratitis), vaccinia, varicella; mycobacterial infections; fungal diseases of the eye, and dacryocystitis.

5 WARNINGS AND PRECAUTIONS

5.1 Intraocular Pressure Increase

Prolonged use of corticosteroids may result in glaucoma with damage to the optic nerve, defects in visual acuity and fields of vision. Steroids should be used with caution in the presence of glaucoma. Intraocular pressure should be monitored during the course of the treatment.

5.2 Bacterial Infection

Corticosteroids may suppress the host response and thus increase the hazard for secondary ocular infections. In acute purulent conditions, steroids may mask infection and enhance existing infection [see Contraindications (4)].

5.3 Viral Infections

Use of ocular steroids may prolong the course and may exacerbate the severity of many viral infections of the eye (including herpes simplex) [see Contraindications (4)].

5.4 Fungal Infections

Fungus invasion must be considered in any persistent corneal ulceration where a steroid has been used or is in use. Fungal culture should be taken when appropriate [see Contraindications (4)].

5.5 Delayed Healing

The use of steroids after cataract surgery may delay healing and increase the incidence of bleb formation.

5.6 Other Potential Corticosteroid Complications

The initial prescription and renewal of the medication order of DEXTENZA should be made by a physician only after examination of the patient with the aid of magnification, such as slit lamp biomicroscopy, and, where appropriate, fluorescein staining. If signs and symptoms fail to improve after 2 days, the patient should be re-evaluated.

6 ADVERSE REACTIONS

The following serious adverse reactions are described elsewhere in the labeling:

- Intraocular Pressure Increase [see Warnings and Precautions (5.1)]
- Bacterial Infection [see Warnings and Precautions (5.2)]
- Viral Infection [see Warnings and Precautions (5.3)]
- Fungal Infection [see Warnings and Precautions (5.4)]
- Delayed Healing [see Warnings and Precautions (5.5)]

6.1 Clinical Trials Experience

Because clinical trials are conducted under widely varying conditions, adverse reaction rates observed in the clinical trials of a drug cannot be directly compared to rates in the clinical trials of another drug and may not reflect the rates observed in practice. Adverse reactions associated with ophthalmic steroids include elevated intraocular pressure, which may be associated with optic nerve damage, visual acuity and field defects, posterior subcapsular cataract formation; delayed wound healing; secondary ocular infection from pathogens including herpes simplex, and perforation of the globe where there is thinning of the cornea or sclera [see Warnings and Precautions (5)].

6.2 Ocular Inflammation and Pain Following Ophthalmic Surgery

DEXTENZA safety was studied in four randomized, vehicle-controlled studies (n = 567). The mean age of the population was 68 years (range 35 to 87 years), 59% were female, and 83% were white. Forty-seven percent had brown iris color and 30% had blue iris color. The most common ocular adverse reactions that occurred in patients treated with DEXTENZA were: anterior chamber inflammation including iritis and iridocyclitis (10%); intraocular pressure increased (6%); visual acuity reduced (2%); cystoid macular edema (1%); corneal edema (1%); eye pain (1%) and conjunctival hyperemia (1%).

The most common non-ocular adverse reaction that occurred in patients treated with DEXTENZA was headache (1%).

6.3 Itching Associated with Allergic Conjunctivitis

DEXTENZA safety was studied in four randomized, vehicle-controlled studies (n= 154). The mean age of the population was 41 years (range 19 to 69 years), 55 % were female and 61 % were white. Fifty seven percent had brown iris color and 20% had blue iris color. The most common ocular adverse reactions that occurred in patients treated with DEXTENZA were: intraocular pressure increased (3%), lacrimation increased (1%), eye discharge (1%), and visual acuity reduced (1%).

The most common non-ocular adverse reaction that occurred in patients treated with DEXTENZA was headache (1%).

8 USE IN SPECIFIC POPULATIONS

8.1 Pregnancy

Risk Summary

There are no adequate or well-controlled studies with DEXTENZA in pregnant women to inform a drug-associated risk for major birth defects and miscarriage. In animal reproduction studies, administration of topical ocular dexamethasone to pregnant mice and rabbits during organogenesis produced embryofetal lethality, cleft palate and multiple visceral malformations (see Data).

Data

Animal Data

Topical ocular administration of 0.15% dexamethasone (0.75 mg/kg/day) on gestational days 10 to 13 produced embryofetal lethality and a high incidence of cleft palate in a mouse study. A daily dose of 0.75 mg/kg/day in the mouse is approximately 5 times the entire dose of dexamethasone in the DEXTENZA product, on a mg/m^2 basis. In a rabbit study, topical ocular administration of 0.1% dexamethasone throughout organogenesis (0.36 mg /day, on gestational day 6 followed by 0.24 mg/day on gestational days 7-18) produced intestinal anomalies, intestinal aplasia, gastroschisis and hypoplastic kidneys. A daily dose of 0.24 mg/day is approximately 6 times the entire dose of dexamethasone in the DEXTENZA product, on a mg/m^2 basis.

8.2 Lactation

Systemically administered corticosteroids appear in human milk and could suppress growth and interfere with endogenous corticosteroid production; however the systemic concentration of dexamethasone following administration of DEXTENZA is low [see Clinical Pharmacology (12.3)]. There is no information regarding the presence of DEXTENZA in human milk, the effects of the drug on the breastfed infant or the effects of the drug on milk production to inform risk of DEXTENZA to an infant during lactation. The developmental and health benefits of breastfeeding should be considered along with the mother's clinical need for DEXTENZA and any potential adverse effects on the breastfed child from DEXTENZA.

8.4 Pediatric Use

The safety and effectiveness of DEXTENZA for the treatment of ocular inflammation and pain following ophthalmic surgery have been established in pediatric patients.

The safety and effectiveness of DEXTENZA for the treatment of ocular itching associated with allergic conjunctivitis have been established in pediatric patients aged 2 years and older. The use of DEXTENZA is not recommended for the treatment of ocular itching associated with allergic conjunctivitis in pediatric patients who require sedation for the insertion procedure.

Use of DEXTENZA for these indications is supported by evidence from adequate and well-controlled studies in adults with additional safety data from a single active-controlled study in pediatric patients aged birth to 5 years old [see Clinical Studies (14)]. A similar safety profile was observed between pediatric and adult patients.

8.5 Geriatric Use

No overall differences in safety or effectiveness have been observed between elderly and younger patients.

11 DESCRIPTION

DEXTENZA (dexamethasone ophthalmic insert) is a fluorescent yellow, 3 mm cylindrical-shaped, resorbable, sterile insert for intracanalicular use. DEXTENZA contains 0.4 mg dexamethasone in a polyethylene glycol (PEG) based hydrogel conjugated with fluorescein. DEXTENZA does not contain an antimicrobial preservative. The active ingredient is represented by the chemical structure:

The chemical name for dexamethasone is 9-Fluoro-11β,17,21-trihydroxy-16α-methylpregna-1,4-diene-3,20-dione. It has a molecular formula of C22H29FO5 and a molecular weight of 392.47 g/mol. Dexamethasone is a crystalline powder.

Each DEXTENZA contains: Active ingredients: 0.4 mg dexamethasone. Inactive ingredients: 4-arm polyethylene glycol (PEG) N-hydroxysuccinimidyl glutarate (20K), trilysine acetate, N-hydroxysuccinimide-fluorescein, sodium phosphate dibasic, sodium phosphate monobasic, water for injection.

12 CLINICAL PHARMACOLOGY

12.1 Mechanism of Action

Dexamethasone, a corticosteroid, has been shown to suppress inflammation by inhibiting multiple inflammatory cytokines resulting in decreased edema, fibrin deposition, capillary leakage and migration of inflammatory cells.

12.3 Pharmacokinetics

Plasma samples were obtained from 16 healthy volunteers prior to insertion of DEXTENZA and on Day 1 (at 1, 2, 4, 8, 16 hours), 2 (24 hours), 4, 8, 15, 22 and 29 following the insertion of DEXTENZA.

Plasma concentrations of dexamethasone were detectable (above 50 pg/mL, the lower limit of quantification of the assay) in 11% of samples (21 of 189), and ranged from 0.05 ng/mL to 0.81 ng/mL.

13 NONCLINICAL TOXICOLOGY

13.1 Carcinogenesis, Mutagenesis, Impairment of Fertility

No adequate studies in animals have been conducted to determine whether DEXTENZA has the potential for carcinogenesis.

Dexamethasone was not mutagenic in the Ames/Salmonella assay, both with and without metabolic activation. Dexamethasone was genotoxic in two in vitro assays using human lymphocytes (chromosomal aberration assay and sister chromatid exchange assay) and was genotoxic in two mouse in vivo assays (micronucleus assay and sister chromatid exchange assay).

Fertility studies have not been conducted in animals using DEXTENZA.

14 CLINICAL STUDIES

14.1 Ocular Inflammation and Pain Following Ophthalmic Surgery

In three randomized, multicenter, double-masked, parallel group, vehicle-controlled efficacy trials, patients received DEXTENZA or its vehicle immediately upon completion of cataract surgery (NCT02034019, NCT02089113, NCT02736175). In all three trials, DEXTENZA had a higher proportion of patients than the vehicle group who were pain free on post-operative Day 8. On post-operative Day 14, in two of the three studies, DEXTENZA had a higher proportion of patients than the vehicle group who had an absence of anterior chamber cells that was statistically significant. Results are shown in Table 1 and Table 2.

Table 1: Percentage of Patients with Absence of Anterior Chamber Cells
 | Study 1 |  |  |  | Study 2 |  |  |  | Study 3
 | dextenza (N=164) | Vehicle (N=83) | Difference (95% CI) |  | dextenza (N=161) | Vehicle (N=80) | Difference (95% CI) |  | Dextenza (N=216) | Vehicle (N=222) | Difference (95% CI)
Visit | n (%) | n (%) | Difference (95% CI) |  | n (%) | n (%) | Difference (95% CI) |  | n (%) | n (%) | Difference (95% CI)
Day 14 | 54 (33%) | 12 (14%) | 18% (8%, 29%) |  | 63 (39%) | 25 (31%) | 8% (-5%, 21%) |  | 113 (52%) | 69 (31%) | 21 % (12%, 30%)

Table 2: Percentage of Patients with Absence of Pain
 | Study 1 |  |  |  | Study 2 |  |  |  | Study 3
 | Dextenza (N=164) | Vehicle (N=83) | Difference (95% CI) |  | Dextenza (N=161) | Vehicle (N=80) | Difference (95% CI) |  | Dextenza (N=216) | Vehicle (N=222) | Difference (95% CI)
Visit | n (%) | n (%) | Difference (95% CI) |  | n (%) | n (%) | Difference (95% CI) |  | n (%) | n (%) | Difference (95% CI)
Day 8 | 131 (80%) | 36 (43%) | 37% (24%, 49%) |  | 124 (77%) | 47 (59%) | 18% (6%, 31%) |  | 172 (80%) | 136 (61%) | 18% (10%, 27%)

14.2 Itching associated with Allergic Conjunctivitis

In three randomized, multicenter, double-masked, parallel group, vehicle-controlled efficacy trials, patients received DEXTENZA or its vehicle utilizing a repeat conjunctival allergen challenge model (NCT02445326, NCT02988882, NCT04050865). In all three trials, DEXTENZA resulted in lower mean ocular itching scores compared with the vehicle group at all time points throughout the one-month duration of the study. In two of the three studies, a higher proportion of patients had statistically significant reductions in ocular itching on Day 8, at 3 minutes, 5 minutes and 7 minutes post-challenge in the DEXTENZA group than in the vehicle group. Results are shown in Table 3.

Table 3: Reduction in Ocular Itching
 |  | Study 1 |  |  |  | Study 2 |  |  |  | Study 3
 |  | Dextenza (N=35) | Vehicle (N=38) | Difference (95% CI) |  | Dextenza (N=44) | Vehicle (N=42) | Difference (95% CI) |  | Dextenza (N=48) | Vehicle (N=48) | Difference (95% CI)
Visit | Time Point | Least Square Means |  | Difference (95% CI) |  | Least Square Means |  | Difference (95% CI) |  | Least Square Means |  | Difference (95% CI)
Day 8 | 3 min | 1.9 | 2.7 | -0.7 (-1.2, -0.3) |  | 2.1 | 2.3 | -0.2 (-0.7, 0.3) |  | 1.8 | 2.7 | -0.9 (-1.2, -0.4)
Day 8 | 5 min | 2.1 | 2.8 | -0.7 (-1.2, -0.3) |  | 2.1 | 2.3 | -0.2 (-0.8, 0.3) |  | 1.8 | 2.7 | -1.0 (-1.4, -0.6)
Day 8 | 7 min | 1.9 | 2.7 | -0.8 (-1.2, -0.4) |  | 2.1 | 2.4 | -0.3 (-0.8, 0.3) |  | 1.7 | 2.7 | -1.0 (-1.4, -0.6)

16 HOW SUPPLIED/STORAGE AND HANDLING

DEXTENZA is supplied sterile in a foam carrier within a foil laminate pouch containing:

NDC 70382-204-10 | Carton containing 10 pouches (10 inserts)
NDC 70382-204-01 | Carton containing 1 pouch (1 insert)

Do not use if pouch has been damaged or broken.

DEXTENZA is intended for single dose only.

STORAGE AND HANDLING

Storage: Store refrigerated, between 2°C and 8°C (36°F and 46°F). Do not freeze. Protect from light, keep in package until use.

17 PATIENT COUNSELING INFORMATION

Advise patients to consult their eye care professional, if pain, redness, or itching develops.

Ocular Therapeutix, Inc.
Bedford, MA 01730 USA

US Patent Nos.: 8,409,606; 8,563,027, 11,458041, 12,144,889, 12,150,896

Principal Display Panel – Dextenza 1 ct Box Label

NDC 70382-204-01

0.4 mg insert

1 insert

Dextenza ®

(dexamethasone ophthalmic insert) 0.4mg

for intracanalicular use

Rx only

Ocular

Therapeutix™

Principal Display Panel – Dextenza 10 ct Box Label

NDC 70382-204-10

0.4 mg insert

10 inserts

Dextenza ®

(dexamethasone ophthalmic insert) 0.4mg

for intracanalicular use

Rx only

Ocular

Therapeutix™

PACKAGE LABEL

Principal Display Panel – Dextenza Sample 1 ct Box Label

NDC 70382-204-99

0.4 mg insert

1 inserts

Dextenza ®

(dexamethasone ophthalmic insert) 0.4mg

for intracanalicular use

Rx only

SAMPLE

Not for resale.

US Patent Nos.

7,648,713 8,409,606 8,563,027 9,254,267

Ocular

Therapeutix™

Principal Display Panel – Dextenza Pouch Label

Dextenza ®

(dexamethasone ophthalmic insert) 0.4mg

for intracanalicular use

Ocular Therapeutix, Inc.

Bedford, MA 01730 USA

NDC 70382-204-88

Rx only

LOT:

EXP DATE:

DIRECTIONS FOR USE: See enclosed package
insert. Do not use if pouch has been damaged
or broken. DEXTENZA is intended for single dose only.

CONTENTS: One DEXTENZA insert in foam carrier.

STORAGE: Refrigerate between 2 ° C - 8 ° C
(36° F - 46° F). Do not freeze. Protect from light,
keep in package until use.

STERILE: Do not re-sterilize.

PCR-780-12173